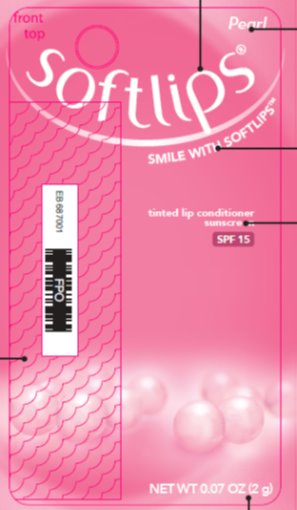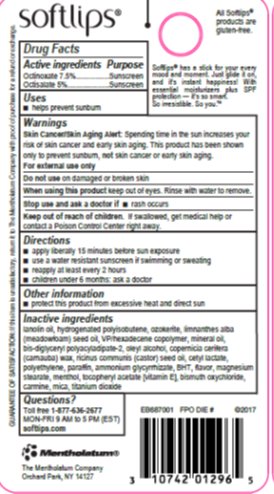 DRUG LABEL: Softlips Pearl
NDC: 10742-8573 | Form: STICK
Manufacturer: The Mentholatum Company
Category: otc | Type: HUMAN OTC DRUG LABEL
Date: 20241217

ACTIVE INGREDIENTS: OCTINOXATE 75 mg/1 g; OCTISALATE 50 mg/1 g
INACTIVE INGREDIENTS: LANOLIN OIL; HYDROGENATED POLYBUTENE (1300 MW); CERESIN; MEADOWFOAM SEED OIL; VINYLPYRROLIDONE/HEXADECENE COPOLYMER; MINERAL OIL; BIS-DIGLYCERYL POLYACYLADIPATE-2; OLEYL ALCOHOL; CARNAUBA WAX; CASTOR OIL; CETYL LACTATE; PARAFFIN; AMMONIUM GLYCYRRHIZATE; BUTYLATED HYDROXYTOLUENE; MAGNESIUM STEARATE; MENTHOL, UNSPECIFIED FORM; .ALPHA.-TOCOPHEROL; BISMUTH OXYCHLORIDE; CARMINIC ACID; MICA; TITANIUM DIOXIDE

Drug Facts - Softlips Pearl

Active ingredients

Octinoxate 7.5%

Octisalate 5%

Purpose

Octinoxate - Sunscreen

Octisalate - Sunscreen

Uses

- helps prevent sunburn

Warnings

Skin Cancer/Skin Aging Alert: Spending time in the sun increases your risk of skin cancer and early skin aging. This product has been shown only to prevent sunburn, not skin cancer or early skin aging.

For external use only

Do not use

on damaged or broken skin

When using this product

keep out of eyes. Rinse with water to remove.

Stop use and ask a doctor if

rash occurs

Keep out of reach of children.

If swallowed, get medical help or contact a Poison Control Center right away.

Directions

- apply liberally 15 minutes before sun exposure
- use a water resistant sunscreen if swimming or sweating
- reapply at least every 2 hours
- children under 6 months: ask a doctor

Other information

- protect this product from excessive heat and direct sun

Inactive ingredients

lanolin oil, hydrogenated polyisobutene, ozokerite, limnanthes alba (meadowfoam) seed oil, VP/hexadecene copolymer, mineral oil, bis-diglyceryl polyacyladipate-2, oleyl alcohol, copernicia cerifera (carnauba) wax, ricinus communis (castor) seed oil, cetyl lactate, polyethylene, paraffin, ammonium glycyrrhizate, BHT, flavor, magnesium stearate, menthol, tocopheryl acetate [vitamin E], bismuth oxychloride, carmine, mica, titanium dioxide

Questions?

Toll free 1-877-636-2677 MON-FRI 9AM-5PM (EST) softlips.com